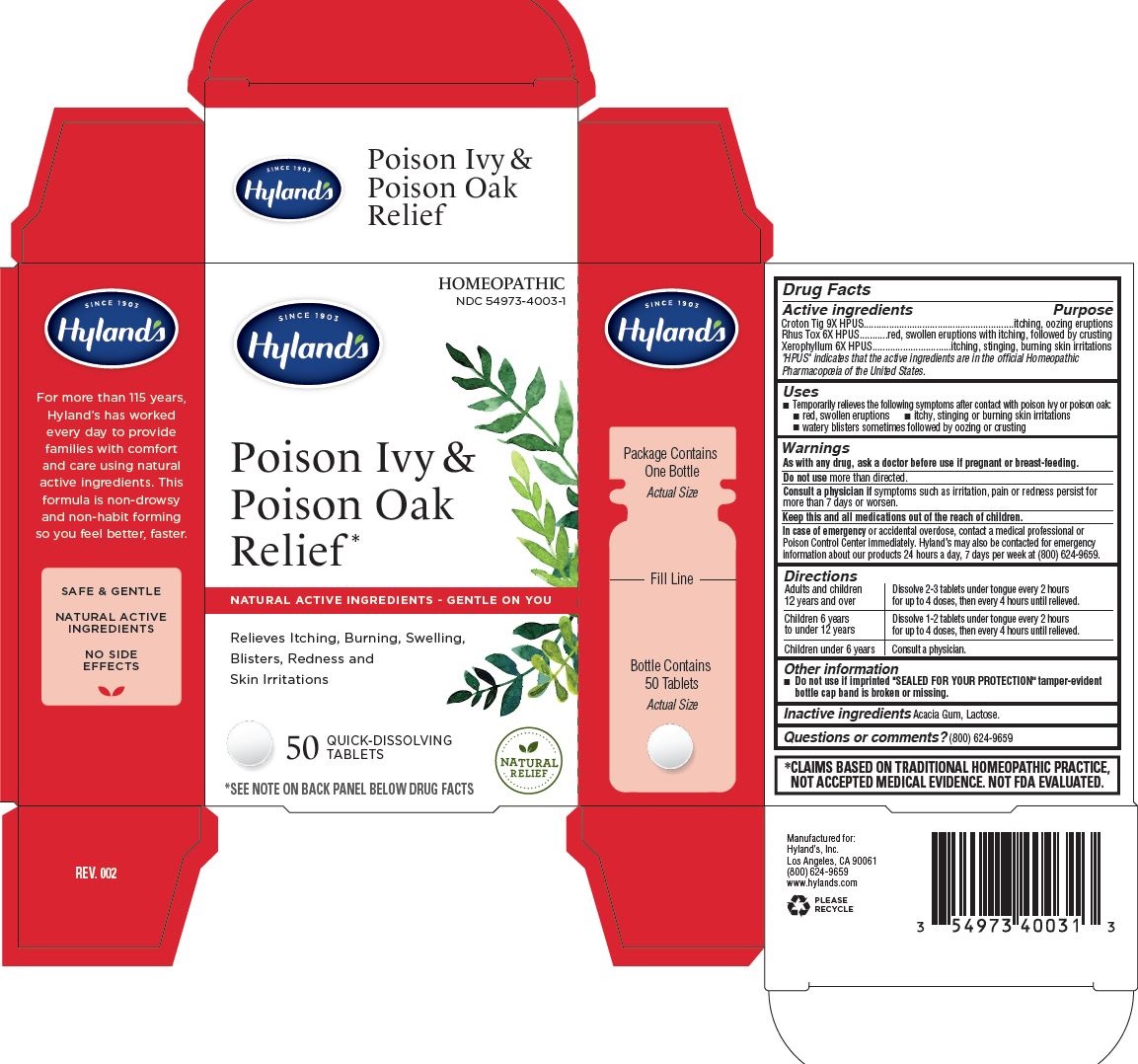 DRUG LABEL: Poison Ivy and Poison Oak Relief
NDC: 54973-4003 | Form: TABLET
Manufacturer: Hyland's Inc.
Category: homeopathic | Type: HUMAN OTC DRUG LABEL
Date: 20221213

ACTIVE INGREDIENTS: TOXICODENDRON PUBESCENS LEAF 6 [hp_X]/1 1; CROTON TIGLIUM SEED 9 [hp_X]/1 1; XEROPHYLLUM ASPHODELOIDES 6 [hp_X]/1 1
INACTIVE INGREDIENTS: ACACIA; LACTOSE MONOHYDRATE

Hyland's Poison Ivy & Poison Oak Relief

PURPOSE

Relieves Itching, Burning, Swelling, Blisters, Redness and Skin Irritations

Drug Facts

Active ingredients | Purpose
Croton Tig 9X HPUS | itching, oozing eruptions
Rhus Tox 6X HPUS | red, swollen eruptions with itching, followed by crusting
Xerophyllum 6X HPUS | itching, stinging, burning skin irritations

"HPUS" indicates that the active ingredients are in the official Homeopathic Pharmacopœia of the United States.

Uses

■Temporarily relieves the following symptoms after contact with poison ivy or poison oak:
■ red, swollen eruptions ■ itchy, stinging or burning skin irritations
■ watery blisters sometimes followed by oozing or crusting

Warnings

PREGNANCY OR BREAST FEEDING

As with any drug, ask a doctor before use if pregnant or breast-feeding.

Do not use more than directed.

ASK DOCTOR

Consult a physician if symptoms such as irritation, pain or redness persist for more than 7 days or worsen.

KEEP OUT OF REACH OF CHILDREN

Keep this and all medications out of the reach of children.

OVERDOSAGE

In case of emergency or accidental overdose, contact a medical professional or Poison Control Center immediately. Hyland’s may also be contacted for emergency information about our products 24 hours a day, 7 days per week at (800) 624-9659.

Directions

Adults and children 12 years and over | Dissolve 2-3 tablets under tongue every 2 hours; for up to 4 doses, then every 4 hours until relieved.
Children 6 years to under 12 years | Dissolve 1-2 tablets under tongue every 2 hours for up to 4 doses, then every 4 hours until relieved.
Children under 6 years | Consult a physician.

Other information

- Do not use if imprinted "SEALED FOR YOUR PROTECTION" tamper-evident bottle cap band is broken or missing.

Inactive ingredients

Acacia Gum, Lactose.

Questions or comments?

(800) 624-9659

*CLAIMS BASED ON TRADITIONAL HOMEOPATHIC PRACTICE, NOT ACCEPTED MEDICAL EVIDENCE. NOT FDA EVALUATED.

Indications and Usage

 Temporarily relieves the following symptoms after contact with poison ivy or poison oak:
 red, swollen eruptions  itchy, stinging or burning skin irritations
 watery blisters sometimes followed by oozing or crusting

Principal Display Panel - 50 Tablets Bottle Carton

HOMEOPATHIC

NDC 54973-4003-1

SINCE 1903

Hyland's

POISON IVY &

POISON OAK

RELIEF*

NATURAL ACTIVE INGREDIENTS - GENTLE ON YOU

Relieves Itching, Burning, Swelling,
Blisters, Redness and
Skin Irritations

50 QUICK-DISSOLVING

TABLETS

NATURAL

RELIEF

*SEE NOTE ON BACK PANEL BELOW DRUG FACTS